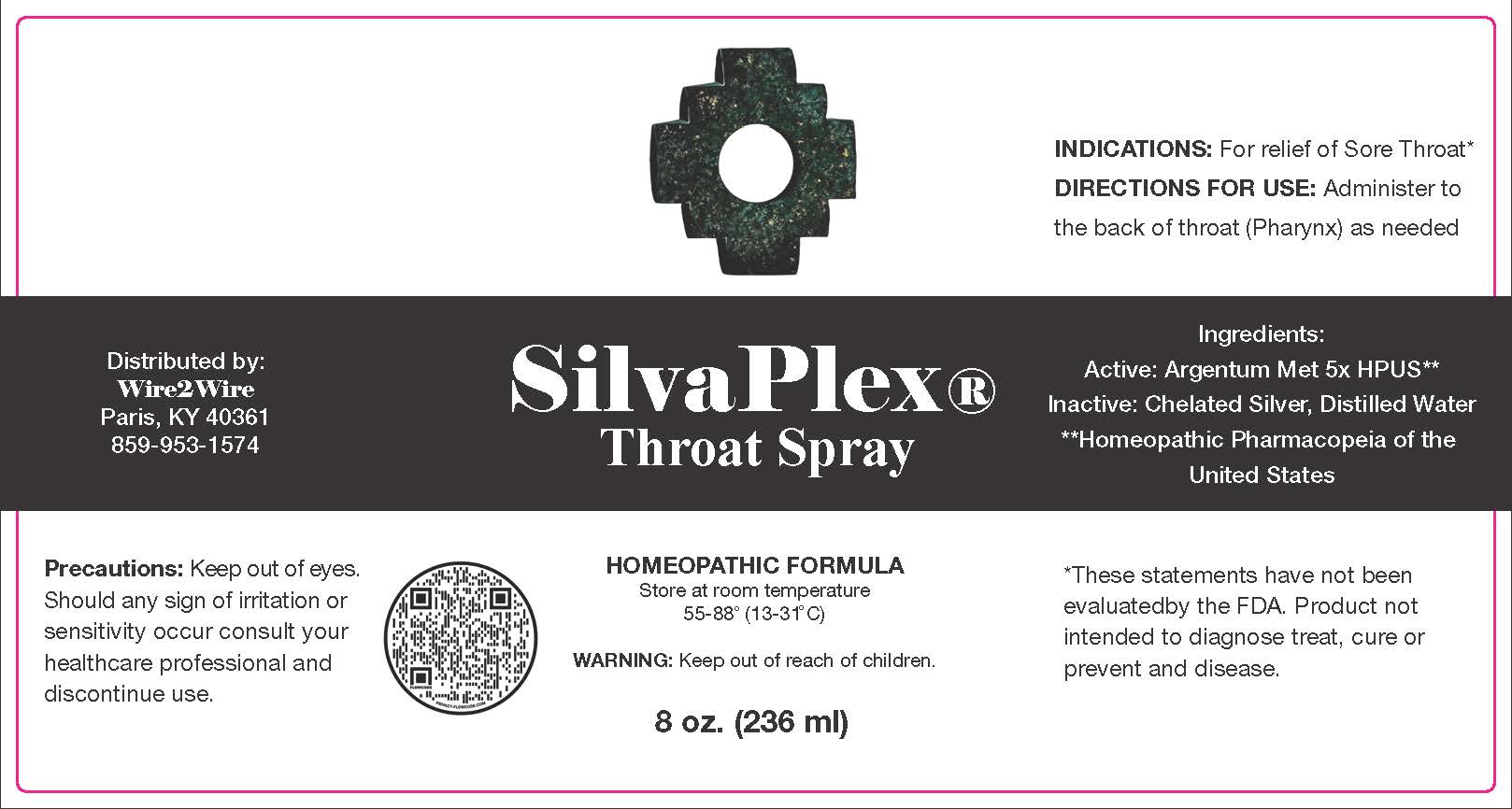 DRUG LABEL: SilvaPlex Throat
NDC: 72363-010 | Form: SPRAY
Manufacturer: AG Essence
Category: homeopathic | Type: HUMAN OTC DRUG LABEL
Date: 20251214

ACTIVE INGREDIENTS: SILVER 0.0003 g/236 g
INACTIVE INGREDIENTS: SILVER OXIDE 0.023 g/236 g; WATER 235.671 g/236 g; CITRIC ACID MONOHYDRATE 0.306 g/236 g

SilvaPlex Throat Spray 8 oz.

DIRECTIONS FOR USE:

Administer to the back of throat (Pharynx) as needed.

WARNING:

Keep out of reach of children.

Precautions:

Keep out of eyes.

Should any sign of irritation or

sensitivity occur consult your

healthcare professional and

discontinue use.

Ingredients:

Active; Argentum Met 5X HPUS**

**Homeopathic Pharmacopeia of the United States

Ingredients:

Inactive: Chelated Silver, Distilled Water

Warning

Keep out of reach of children.